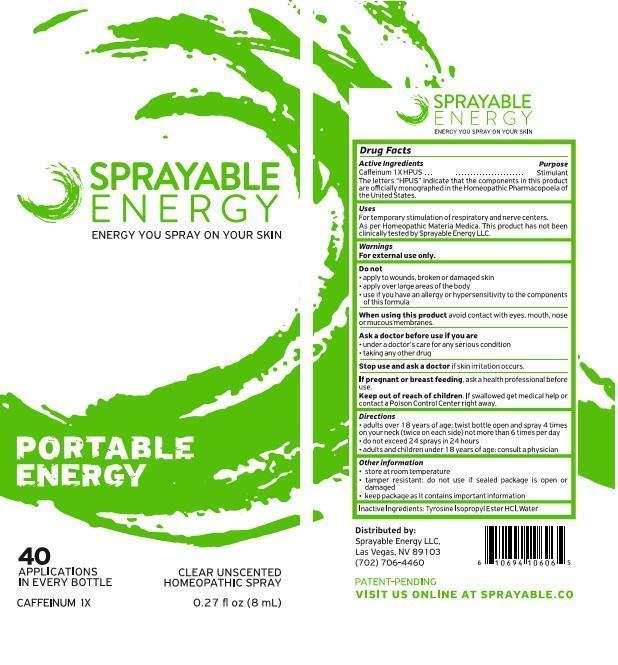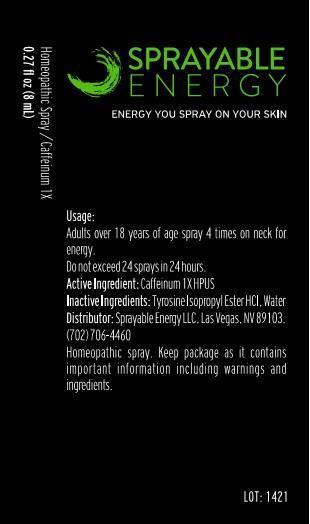 DRUG LABEL: Sprayable Energy
NDC: 59332-001 | Form: SPRAY
Manufacturer: Spayable Energy LLC
Category: homeopathic | Type: HUMAN OTC DRUG LABEL
Date: 20131121

ACTIVE INGREDIENTS: CAFFEINE 1 [hp_X]/8 mL
INACTIVE INGREDIENTS: WATER

Drug Facts

Active Ingredients

Caffeinum 1X HPUS

Purpose

Caffeinum 1X HPUS..........................Stimulant

The letters "HPUS" indicate that the components in this product are officially monographed in the Homeopathic Pharmacopoeia of the United States.

Uses

For temporary stimulation of respiratory and nerve centers.

As per Homeopathic Materia Medica.This product has not been clinically tested by Sprayable Energy LLC.

Warnings

For external use only.

Do not

- apply to wounds, broken or damaged skin
- apply over large areas of the body
- use if you have an allergy or hypersensitivity to the components of this formula

When using this product

avoid contact with eyes, mouth, nose or mucous membranes.

Ask a doctor before use if you are

- under a doctor's care for any serious condition
- taking any other drug

Stop use and ask a doctor

if skin irritation occurs.

If pregnant or breast feeding,

ask a health professional before use.

Keep out of reach of children.

OTHER SAFETY INFORMATION

If swallowed get medical help or contact a Poison Control Center right away.

Directions

- adults over 18 years of age: twist bottle open and spray 4 times on your neck (twice on each side) not more than 6 times per day
- do not exceed 24 sprays in 24 hours
- adults and children under 18 years of age: consult a physician

Other information

- store at room temperature
- tamper resistant: do not use if sealed package is open or damaged
- keep package as it contains important information

Inactive Ingredients:

Tyrosine Isopropyl Ester HCl, Water

DESCRIPTION

Distributed by:

Sprayable Energy LLC,

Las Vegas, NV 89103

(702) 706-4460

PATENT-PENDING

VISIT US ONLINE AT SPRAYABLE. CO

Principal Display Panel

SPRAYABLE

ENERGY

ENERGY YOU SPRAY ON YOUR SKIN

PORTABLE

ENERGY

40

APPLICATIONS CLEAR UNSCENTED

IN EVERY BOTTLE HOMEOPATHIC SPRAY

CAFFEINUM 1X 0.27 fl oz (8 mL)